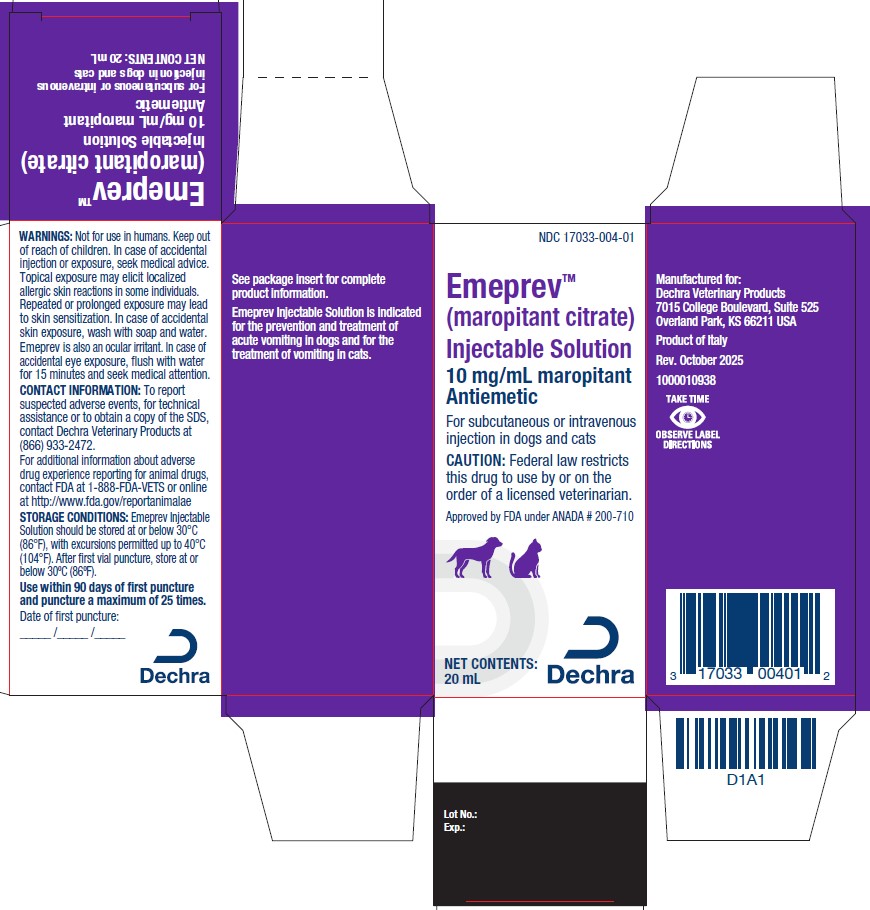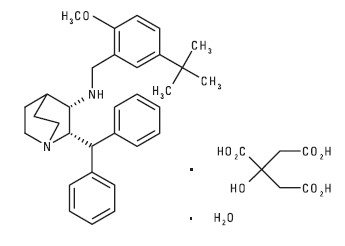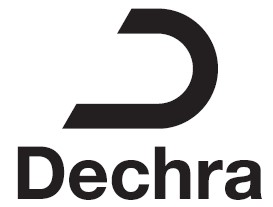 DRUG LABEL: Emeprev
NDC: 17033-004 | Form: INJECTION
Manufacturer: Dechra Veterinary Products, LLC
Category: animal | Type: PRESCRIPTION ANIMAL DRUG LABEL
Date: 20251208

ACTIVE INGREDIENTS: MAROPITANT CITRATE 10 mg/1 mL
INACTIVE INGREDIENTS: BETADEX SULFOBUTYL ETHER SODIUM 63 mg/1 mL; BENZYL ALCOHOL 11.1 mg/1 mL; WATER

Emeprev™
(maropitant citrate)
Injectable Solution

Antiemetic

For subcutaneous or intravenous injection in dogs and cats

CAUTION:

Federal law restricts this drug to use by or on the order of a licensed veterinarian.

DESCRIPTION:

Maropitant is a neurokinin (NK1) receptor antagonist that blocks the pharmacological action of substance P in the central nervous system (CNS).

Maropitant is the non-proprietary designation for a substituted quinuclidine. The empirical formula is C32H40N2O C6H8O7 H2O and the molecular weight 678.81. The chemical name is (2S,3S)-2-benzhydryl-N-(5-tert-butyl-2-methoxybenzyl) quinuclidin-3-amine citrate monohydrate. Each mL of Maropitant Citrate Injectable Solution contains 10 mg maropitant, 63 mg sulphobutylether-beta-cyclodextrin, 11.1 mg benzyl alcohol and water for injection. Sodium hydroxide or citric acid may be added to adjust pH.

The chemical structure of maropitant citrate is:

INDICATIONS:

Dogs: Emeprev (maropitant citrate) Injectable Solution is indicated for the prevention and treatment of acute vomiting in dogs.

Cats: Emeprev (maropitant citrate) Injectable Solution is indicated for the treatment of vomiting in cats.

DOSAGE AND ADMINISTRATION:

Use of refrigerated product may reduce the pain response associated with subcutaneous injection.

Dogs:

For Prevention and Treatment of Acute Vomiting in Dogs:

Dogs 2-4 Months of Age: Administer Emeprev Injectable Solution subcutaneously at 1 mg/kg (0.45 mg/lb) equal to 0.1 mL/kg (0.1 mL/2.2 lb) of body weight once daily for up to 5 consecutive days.

Dogs 4 months of Age and Older: Administer Emeprev Injectable Solution intravenously over 1-2 minutes or subcutaneously at 1 mg/kg (0.45 mg/lb) equal to 0.1 mL/1 kg (1 mL/22 lb) of body weight once daily for up to 5 consecutive days.

In dogs that are actively vomiting, it is recommended to initiate treatment with Emeprev Injectable Solution. Thereafter, maropitant citrate tablets may be used for the prevention of acute vomiting at 2 mg/kg once daily. (See maropitant citrate tablet package insert for complete prescribing information).

For Prevention of Vomiting in Dogs 4 months of Age and Older Caused by Emetogenic Medications or Chemotherapeutic Agents: Administer Emeprev Injectable Solution intravenously over 1-2 minutes or subcutaneously at 1 mg/kg (0.45 mg/lb) of body weight one time, 45-60 minutes prior to use of emetogenic medications or chemotherapeutic agents.

Cats:

For Treatment of Vomiting in Cats 4 Months of Age and Older: Administer Emeprev Injectable Solution intravenously over 1-2 minutes or subcutaneously at 1 mg/kg (0.45 mg/lb) equal to 0.1 mL/kg (0.1 mL/2.2 lb) of body weight once daily for up to 5 consecutive days.

The underlying cause of acute vomiting should be identified and addressed in dogs and cats that receive Emeprev Injectable Solution. If vomiting persists despite treatment, the case should be re-evaluated.

WARNINGS:

Not for use in humans. Keep out of reach of children. In case of accidental injection or exposure, seek medical advice. Topical exposure may elicit localized allergic skin reactions in some individuals. Repeated or prolonged exposure may lead to skin sensitization. In case of accidental skin exposure, wash with soap and water. Emeprev Injectable Solution is also an ocular irritant. In case of accidental eye exposure, flush with water for 15 minutes and seek medical attention.

In puppies younger than 11 weeks of age, histological evidence of bone marrow hypocellularity was observed at higher frequency and greater severity in puppies treated with maropitant citrate compared to control puppies. In puppies 16 weeks and older, bone marrow hypocellularity was not observed (see ANIMAL SAFETY).

PRECAUTIONS:

The safe use of Emeprev Injectable Solution has not been evaluated in dogs or cats with gastrointestinal obstruction or that have ingested toxins.

Use with caution in patients with hepatic dysfunction because Emeprev Injectable Solution is metabolized by CYP3A, CYP2D15 (dogs) and CYP1A (cats) enzymes (see Pharmacokinetics). The influence of concomitant drugs that may inhibit the metabolism of Emeprev Injectable Solution has not been evaluated. Emeprev Injectable Solution is highly protein bound. Use with caution with other medications that are highly protein bound. The concomitant use of Emeprev Injectable Solution with other protein bound drugs has not been studied in dogs or cats. Commonly used protein bound drugs include NSAIDs, cardiac, anticonvulsant, and behavioral medications. Drug compatibility should be monitored in patients requiring adjunctive therapy.

The safe use of Emeprev Injectable Solution has not been evaluated in dogs or cats used for breeding, or in pregnant or lactating bitches or queens.

ADVERSE REACTIONS:

DOGS

In a US field study for the prevention and treatment of vomiting associated with administration of cisplatin for cancer chemotherapy, the following adverse reactions were reported in 77 dogs treated with maropitant citrate injectable solution at 1 mg/kg subcutaneously or 41 dogs treated with placebo:

Frequency of Adverse Reactions by Treatment
Adverse Reaction | Placebo (n=41) |  | maropitant citrate (n=77)
Adverse Reaction | # dogs | % occur | # dogs | % occur
Diarrhea | 1 | 2.4 | 6 | 7.8
Anorexia | 0 | 0 | 4 | 5.2
Injection site reaction; (swelling, pain upon injection) | 0 | 0 | 3 | 4
Lethargy | 1 | 2.4 | 2 | 2.6

The following adverse reactions were reported during the course of a US field study for the prevention and treatment of acute vomiting in dogs treated with 1 mg/kg maropitant citrate injectable solution subcutaneously and/or maropitant citrate tablets at a minimum of 2 mg/kg orally once daily for up to 5 consecutive days:

Frequency of Adverse Reactions by Treatment
Adverse Reaction | Placebo (n=69) |  | maropitant citrate (n=206)
Adverse Reaction | # dogs | % occur | # dogs | % occur
Death during study | 4 | 5.8 | 10 | 4.9
Euthanized during study | 0 | 0 | 2 | 1
Diarrhea | 6 | 8.7 | 8 | 3.9
Hematochezia/bloody stool | 5 | 7.2 | 4 | 1.9
Anorexia | 2 | 2.9 | 3 | 1.5
Otitis/Otorrhea | 0 | 0 | 3 | 1.5
Endotoxic Shock | 1 | 1.4 | 2 | 1
Hematuria | 0 | 0 | 2 | 1
Excoriation | 0 | 0 | 2 | 1

Other clinical signs were reported but were <0.5% of dogs.
Adverse reactions seen in a European field study included ataxia, lethargy and injection site soreness in one dog treated with maropitant citrate injectable solution.

Post-Approval Experience (Rev. 2015)
The following adverse events are based on post-approval adverse drug experience reporting. Not all adverse events are reported to FDA CVM. It is not always possible to reliably estimate the adverse event frequency or establish a causal relationship to product exposure using these data.

The following adverse events reported for dogs are listed in decreasing order of reporting frequency for maropitant citrate injectable solution: Pain/vocalization upon injection, depression/lethargy, anorexia, anaphylaxis/anaphylactoid reactions (including swelling of the head/face), ataxia, convulsions, hypersalivation, tremors, fever, dyspnea, collapse/loss of consciousness, recumbency, injection site reactions (swelling, inflammation) and sedation.

Cases of death (including euthanasia) have been reported.

CATS

The following adverse reactions were reported during the course of a US field study for the treatment of vomiting in cats treated with 1 mg/kg maropitant citrate injectable solution subcutaneously once daily for up to five consecutive days:

Frequency of Adverse Reactions by Treatment
Adverse Reaction | Placebo (n=62) |  | maropitant citrate (n=133)
Adverse Reaction | # cats | % occur | # cats | % occur
Moderate Response to Injection*,† | 1 | 1.6 | 30 | 22.6
Significant Response to Injection*,‡ | 1 | 1.6 | 15 | 11.3
Fever/Pyrexia | 2 | 3.2 | 2 | 1.5
Dehydration | 0 | 0 | 3 | 2.3
Lethargy | 0 | 0 | 2 | 1.5
Anorexia | 0 | 0 | 1 | 0.8
Hematuria | 0 | 0 | 1 | 0.8
Hypersalivation | 0 | 0 | 1 | 0.8
Injection Site Swelling | 1 | 1.6 | 0 | 0
* The clinician observed and graded each cat's response to injection.
† Cat objected to the injection by retreating and vocalizing
‡ Cat objected to the injection by retreating, hissing, scratching, and vocalization

Post-Approval Experience (Rev. 2015)
The following adverse events are based on post-approval adverse drug experience reporting. Not all adverse events are reported to FDA CVM. It is not always possible to reliably estimate the adverse event frequency or establish a causal relationship to product exposure using these data.

The following adverse events reported for cats are listed in decreasing order of reporting frequency for maropitant citrate injectable solution: Depression/lethargy, anorexia, hypersalivation, pain/vocalization upon injection, dyspnea, ataxia, fever, recumbency, vomiting, panting, convulsion, and muscle tremor.

Cases of death (including euthanasia) have been reported.

CONTACT INFORMATION:
To report suspected adverse drug events, for technical assistance, or to obtain a copy of the Safety Data Sheet, contact Dechra Veterinary Products at (866) 933-2472.

For additional information about adverse drug experience reporting for animal drugs, contact FDA at 1-888-FDA-VETS or http://www.fda.gov/reportanimalae

CLINICAL PHARMACOLOGY:

Pharmacodynamics:

Vomiting is a complex process coordinated centrally by the emetic center which consists of several brainstem nuclei (area postrema, nucleus tractus solitarius, dorsal motor nucleus of the vagus) that receive and integrate sensory stimuli from central and peripheral sources and chemical stimuli from the circulation and the cerebro-spinal fluid. Maropitant is a neurokinin 1 (NK1) receptor antagonist which acts by inhibiting the binding of substance P, a neuropeptide of the tachykinin family. Substance P is found in significant concentrations in the nuclei comprising the emetic center and is considered the key neurotransmitter involved in emesis.^1 By inhibiting the binding of substance P within the emetic center, maropitant provides broad-spectrum effectiveness against neural (central) and humoral (peripheral) causes of vomiting. In vivo model studies in dogs have shown that maropitant has antiemetic effectiveness against both central and peripheral emetogens including apomorphine, cisplatin, and syrup of ipecac.

Pharmacokinetics:

Maropitant citrate injectable solution is formulated using sulphobutylether-ß-cyclodextrin (SBECD), which exhibits enhanced binding to maropitant at refrigerated temperatures. The enhanced binding affinity reverses rapidly upon warming.

DOGS

The pharmacokinetic (PK) characterization associated with maropitant after a single oral (PO), intravenous (IV), or subcutaneous (SC) dose administration in adult Beagle dogs is provided in the table below.

Pharmacokinetic Parameters in Beagle Dogs(Mean ±SD or Mean and Range)
PK Parameter | SC at 1 mg/kg (n=8) | IV at 1 mg/kg (n=8) | PO at 2 mg/kg (n=8) | PO at 8 mg/kg (n=8)
AUC0-inf (hr*ng/mL) | 759.08±189.49 | 693.83±137.25 | 561±322 | 7840±5600
Cmax (ng/mL) | 102.99±46.06 | 296.62±60.77 | 81±32 | 776±604
T1/2 (hr) | 8.84a (6.15-20.48) | 6.85a (4.87 -11.30) | 4.03 (2.48– 7.09) | 5.46 (3.39–7.65)
Tmax (hr) | 0.56±0.40 | n/a | 1.9±0.5 | 1.7±0.7
a Harmonic mean

The absolute bioavailability of maropitant was much higher following SC injection (91% at 1 mg/kg) than after PO administration (24% at 2 mg/kg). Oral bioavailability may be underestimated due to the presence of nonlinear kinetics and the resulting longer T1/2 seen after intravenous (IV) administration. Although hepatic first-pass metabolism contributed to the relatively low bioavailability after an oral dose, prandial status does not significantly affect the extent of oral bioavailability. Greater than dose-proportional drug exposure can be expected with an increase in dose (116 mg/kg PO). Systemic clearance of maropitant following IV administration was 1499.13 mL/hr/kg at a dose of 1 mg/kg. An accumulation ratio of 1.5 was observed following once-daily use of maropitant for five consecutive days at 1 (SC) or 2 mg/kg (PO). Urinary recovery of maropitant and its major metabolite was minimal (<1% each). The hepatic metabolism of maropitant involves two cytochrome P-450 isoenzymes: CYP2D15 and CYP3A12. Based on in vitro enzyme kinetics data, it is believed that the non-linear kinetics may be partially associated with saturation of the low capacity enzyme (CYP2D15). However as doses increase (2050 mg/kg PO), dose proportionality is re-established.

Based upon in vitro enzyme kinetics, involvement of a high capacity enzyme (CYP3A12) may contribute to this return to dose linearity. Plasma protein binding of maropitant was high (99.5%).

Based on differences in plasma trough concentrations from a single study, the exposure of 10 week old puppies to maropitant may be lower than that observed in adult dogs, particularly after doses of 1 or 2 mg/kg.

CATS

The pharmacokinetic characterization associated with maropitant after a single subcutaneous (SC) or intravenous (IV) dose administration in cats is provided in the table below.

Pharmacokinetic Parameters for a Single Dose in 6-7 Month Old Cats (Mean±SD or Mean and Range)
PK Parameter | SC at 1 mg/kg (n=6) | IV at 1 mg/kg (n=6)
AUC0-inf (hr*ng/mL) | 2016.07±516.65 | 2116.53±706.72
Cmax (ng/mL) | 257.84±49.95 | 987.65±421.75
T1/2 (hr) | 6.57a (5.09-8.60) | 4.86a (3.44-6.79)
Tmax (hr) | 0.43±0.33 | n/a
a Harmonic mean

There appears to be an age-related effect on the pharmacokinetics of maropitant in cats; kittens (4 months) have a higher clearance than adults. In multiple IV and SC studies, the mean maropitant half-life in kittens (4-7 months old) is 7.83 hours, compared to 17.2 hours in adults. The mean bioavailability of maropitant after subcutaneous administration in cats was 91.3%. The mean total body clearance (CL) and volume of distribution at steady-state (Vss) determined after IV administration of 1.0 mg/kg to 6 cats was 510 (388 to 603) mL/hr/kg and 2.3 (1.4 to 3.6) L/kg, respectively. Maropitant displays linear kinetics when administered SC within the 0.25–3 mg/kg dose range. Following SC administration of once daily doses of 1 mg/kg body weight for 5 consecutive days, accumulation was 250%. Maropitant undergoes cytochrome P450 (CYP) metabolism in the liver. CYP1A and CYP3A-related enzymes were identified as the feline isoforms involved in the hepatic biotransformation of maropitant. Renal and fecal clearances are minor routes of elimination for maropitant, with less than 1% of a 1 mg/kg SC dose appearing in the urine or feces as maropitant. For the major metabolite, 10.4% of the maropitant dose was recovered in urine and 9.3% in feces. Plasma protein binding of maropitant in cats was estimated to be 99.1%.

EFFECTIVENESS:

DOGS:

In laboratory model studies, maropitant citrate injectable solution administered subcutaneously at 1 mg/kg in Beagle dogs reduced the number of emetic events associated with established neural (central) and humoral (peripheral) stimuli. Following administration of apomorphine (central emetic stimuli), vomiting was observed in 16.7% (2 of 12) of dogs treated with maropitant citrate injectable solution and 83.3% (10 of 12) of placebo-treated dogs. Following administration of syrup of ipecac (peripheral emetic stimuli) vomiting was observed in 25% (3 of 12) of dogs treated with maropitant citrate injectable solution and in 100% (12 of 12) of dogs treated with placebo.

In a study of veterinary cancer patients, dogs were treated with maropitant citrate injectable solution or placebo either 1 hour prior to cisplatin (prevention) or after the first vomiting episode following cisplatin (treatment) and monitored for 5 hours. In the groups evaluated for prevention of vomiting, 94.9% (37/39) of the dogs administered maropitant citrate injectable solution and 4.9% (2/41) of the dogs administered placebo did not vomit. In the groups evaluated for treatment, 21% (8/38) of the dogs administered maropitant citrate injectable solution and 5.1% (2/39) of the dogs administered placebo had no further episodes of vomiting following treatment.

Frequency Distribution of Numbers of Vomiting Episodes For Treatment: Number of Vomiting Episodes Post Injection. For Prevention: Total Number of Vomiting Episodes.
Number of; Vomiting Episodes | Dogs with Vomiting Episodes * (% of Dogs)
Number of; Vomiting Episodes | Treatment of Vomiting |  | Prevention of Vomiting
Number of; Vomiting Episodes | Placebo (n=39†) | maropitant citrate (n=38†) | Placebo (n=41) | maropitant citrate (n=39)
0 | 2 (5.1) | 8 (21.1) | 2 (4.9) | 37 (94.9)
1 | 3 (7.7) | 7 (18.4) | 2 (4.9) | 1 (2.6)
2 | 4 (10.3) | 6 (15.8) | 3 (7.3) | 1 (2.6)
3 | 3 (7.7) | 6 (15.8) | 4 (9.8) | 0 (0)
4 | 4 (10.3) | 4 (10.5) | 3 (7.3) | 0 (0)
5 | 2 (5.1) | 5 (13.2) | 4 (9.8) | 0 (0)
6 | 14 (35.9) | 1 (2.6) | 1 (2.4) | 0 (0)
7 | 2 (5.1) | 1 (2.6) | 12 (29.3) | 0 (0)
8 | 2 (5.1) | 0 (0) | 5 (12.2) | 0 (0)
9 | 2 (5.1) | 0 (0) | 2 (4.9) | 0 (0)
10 | 0 (0) | 0 (0) | 2 (4.9) | 0 (0)
11 | 1 (2.6) | 0 (0) | 0 (0) | 0 (0)
12 | NA | NA | 1 (2.4) | 0 (0)
* Dogs that exhibited an unacceptable level of vomiting (6 events) were withdrawn from the study and treated with another antiemetic.
† There were initially 41 and 42 dogs treated with either placebo or maropitant citrate injectable solution, respectively. However, if a dog did not vomit following cisplatin therapy, it did not receive a post-cisplatin treatment with either placebo or maropitant citrate, and hence it was not considered in thetherapeutic evaluation.

In a study of 275 canine patients presented to veterinary hospitals with a history of acute vomiting, dogs were initially administered maropitant citrate injectable solution or placebo on Day 0. Following the initial dose, dogs allocated to the maropitant citrate group were treated with either maropitant citrate tablets at a minimum of 2 mg/kg orally or maropitant citrate injectable solution at 1 mg/kg subcutaneously once daily at the discretion of the clinician. Dogs allocated to the placebo group were treated using either an injectable placebo solution or placebo tablets once daily at the discretion of the clinician. Of the 199 dogs included in the analysis for effectiveness, 27 of 54 dogs (50%) in the placebo group displayed vomiting at some time during the study and 31 of 145 dogs (21.4%) in the maropitant citrate-treated group displayed vomiting during the study period.

Percent of Vomiting for Each Study Day, Based Upon Treatment and Route of Administration.
Days | Treatment | Route | # dogs | # vomited | % vomited
Day 0 | Placebo (54) | SC | 54 | 15 | 28%
Day 0 | maropitant citrate (145) | SC | 145 (143*) | 14 | 10%
Day 1 | Placebo (45) | PO | 22 | 3 | 14%
Day 1 | Placebo (45) | SC | 23 | 16 | 70%
Day 1 | maropitant citrate (108) | PO | 67 | 2 | 3%
Day 1 | maropitant citrate (108) | SC | 41 | 16 | 39%
Day 2 | Placebo (16) | PO | 7 | 2 | 29%
Day 2 | Placebo (16) | SC | 9 | 6 | 67%
Day 2 | maropitant citrate (37) | PO | 24 | 0 | 0%
Day 2 | maropitant citrate (37) | SC | 13 | 8 | 62%
Day 3 | Placebo (6) | PO | 2 | 0 | 0%
Day 3 | Placebo (6) | SC | 4 | 1 | 25%
Day 3 | maropitant citrate (21) | PO | 14 | 0 | 0%
Day 3 | maropitant citrate (21) | SC | 7 | 5 | 71%
Day 4 | Placebo (2) | PO | 1 | 0 | 0%
Day 4 | Placebo (2) | SC | 1 | 1 | 100%
Day 4 | maropitant citrate (7) | PO | 5 | 0 | 0%
Day 4 | maropitant citrate (7) | SC | 2 | 1 | 50%
Day 5 | maropitant citrate (1) | SC | 1 | 0 | 0%
* 2 dogs administered maropitant citrate injectable solution were not observed on Day 0. Their vomiting status was unknown. 143 was used in the denominator for % vomited.

In US field studies in veterinary patients, maropitant citrate injectable solution and tablets were well tolerated in dogs presenting with various clinical conditions including parvovirus, gastroenteritis, and renal disease. There were no notable differences in mean laboratory values between maropitant citrate-treated and placebo-treated patients.

Maropitant citrate injectable solution was used safely in dogs receiving other frequently used veterinary products such as fluid and electrolyte replacement solutions, antimicrobial agents, vaccines, antacids, and antiparasitic agents.

In a laboratory study, thirty-one dogs were subcutaneously administered maropitant citrate injectable solution or saline, at 1 mL/10 kg body weight, 45 minutes prior to administration of an opioid analgesic. Following administration of the opioid analgesic, none of the maropitant citrate injectable solution treated dogs vomited and 93.8% (15/16) of placebo-treated dogs vomited.

The effectiveness of maropitant citrate injectable solution administered at 1 mg/kg IV was demonstrated by bridging the results of a PK study to clinical data supporting effectiveness of 1 mg/kg administered SC. The IV and SC administration of a single dose of 1 mg/kg maropitant are equivalent, based on the bioequivalence of the IV and SC AUClast and justification for the therapeutic equivalence of the IV and SC Cmax.

CATS:

In a field study, 195 cats were presented to veterinary hospitals with a history of vomiting associated with various clinical conditions including gastroenteritis, gastritis, pancreatitis, inflammatory bowel disease, neoplasia, and hepatic lipidosis. Cats were treated with maropitant citrate injectable solution or placebo (in a ratio of 2:1) and observed in the veterinary hospital for 24 hours for the presence of an emetic event(s) defined as the observation of the act of vomiting or the presence of vomitus. Cats could continue antiemetic treatment every 24 hours for up to 5 consecutive days at the discretion of the clinician. Of 165 cats included in the analysis for effectiveness, 2 maropitant citrate injectable solution treated cats (1.8%) vomited 1 time each and 10 placebo-treated cats (18.5%) vomited a total of 15 times in the first 24 hours post treatment.

Percent of Cats Vomiting for Each Study Day by Treatment
Study Day | Treatment | # cats | # vomited | % vomited
Day 0 | Placebo | 54 | 10 | 18.5
Day 0 | maropitant citrate | 111 | 2 | 1.8
Day 1 | Placebo | 20 | 4 | 20.0
Day 1 | maropitant citrate | 34 | 1 | 2.9
Day 2 | Placebo | 9 | 2 | 22.2
Day 2 | maropitant citrate | 8 | 0 | 0
Day 3 | Placebo | 5 | 0 | 0
Day 3 | maropitant citrate | 5 | 0 | 0
Day 4 | Placebo | 3 | 0 | 0
Day 4 | maropitant citrate | 1 | 0 | 0

The effectiveness of maropitant citrate injectable solution administered at 1 mg/kg IV was demonstrated by bridging the results of a PK study to clinical data supporting effectiveness of 1 mg/kg administered SC. The IV and SC administration of a single dose of 1 mg/kg maropitant are equivalent, based on the bioequivalence of the IV and SC AUClast and justification for the therapeutic equivalence of the IV and SC Cmax.

ANIMAL SAFETY

DOGS

Laboratory and field studies have demonstrated that maropitant citrate injectable solution is well tolerated in dogs after subcutaneous administration.

Fifty six Beagle dogs (28 males and 28 females) approximately 16 weeks of age were administered maropitant citrate injectable solution subcutaneously once daily for 15 days at 0, 1, 3, and 5 mg/kg. There were 8 dogs (4 males and 4 females) in the 1 mg/kg group and 16 dogs (8 males and 8 females) in all other groups. The primary treatment-related findings were injection site reactions. Swelling, thickened skin, or pain at one or more of the injection sites on one or more days of the study were observed in 6 of 16 animals treated with 3 mg/kg/day and 5 of 16 animals treated with 5 mg/kg/day. Additionally, the activated partial thromboplastin time (APTT) was prolonged (67.5 seconds, reference range 9-15 seconds) in one male dog in the 1 mg/kg group on study day 15. Relationship of the prolonged APTT to drug administration could not be determined.

Beagle dogs approximately 8 weeks of age were administered maropitant citrate injectable solution subcutaneously once daily for 15 days at 0, 1, 3, and 5 mg/kg using a protocol similar to the previous study. A dose dependent increase in frequency and severity of bone marrow hypoplasia was observed histologically. One placebo-treated dog died on day 14 of the study and was diagnosed with suppurative pancreatitis and esophagitis. Interpretation of the study results is complicated by the health status of study animals. Dogs used in the study were weaned early, minimally acclimated to the test facility, and many of the dogs in the study tested positive for coccidia.

Beagle dogs approximately 10 weeks of age were administered either placebo tablets for 2 days, maropitant citrate tablets at 8 mg/kg for 2 days, placebo (saline) subcutaneously (SC) for 5 days, maropitant citrate injectable solution at 1 mg/kg SC for 5 days, or maropitant citrate tablets at 2 mg/kg for 5 days (8 dogs in each dose group). Mild pain associated with injection was noted in more dogs and lasted longer in dogs that received maropitant injections compared to saline. Males administered maropitant citrate tablets at 8 mg/kg orally for 2 days had a decrease in food consumption. Body weight and food consumption were variable throughout the 4 week acclimatization period. Two dogs that received 8 mg/kg maropitant orally for 2 days were below the reference range for reticulocyte counts. Decreases in reticulocyte counts were also seen in 4 (of 8) placebo treated dogs (SC saline for 5 days). Hypocellular femoral bone marrow described as "minimal" was seen in 1 male that received 1 mg/kg maropitant SC for 5 days; reticulocyte counts were not available for this dog.

Twenty four Beagle dogs approximately 16 weeks of age were administered maropitant citrate injectable solution intravenously once daily for 5 days at 0, 1, and 3 mg/kg (4 females and 4 males per group). Maropitant citrate injectable solution was administered at room temperature over 1-2 minutes. Reaction to injection was not specifically recorded. One male dog in the 1 mg/kg group had low hematocrit and white blood cell count on study day 5. One female dog in the 3 mg/kg group had an increased fibrinogen on study day 5. There were no other clinically relevant findings during the study, at necropsy or in histopathology.

CATS

Thirty-two domestic short hair cats (16 males and 16 females) approximately 16 weeks of age were administered maropitant citrate injectable solution subcutaneously once daily for 15 days at 0, 1, 3, and 5 mg/kg. There were 8 cats (4 males and 4 females) in each group. Treatment-related, dose dependent findings included pain associated with injection of maropitant citrate injectable solution and injection site heat, pain, redness, and firmness. Pain on injection was observed in 5% of cats at 0 mg/kg, 50% of cats at 1 mg/kg, and 75% of cats at 3 and 5 mg/kg. Injection site firmness >10 mm in diameter was observed at one or more of the injection sites, on one or more days of the study, in 1 of 8 cats at 1 mg/kg, 7 of 8 cats at 3 mg/kg, and 7 of 8 cats at 5 mg/kg. There was a statistically significant reduction (p=0.0171) in food intake at 5 mg/kg compared to cats at 0 mg/kg. One cat at 5 mg/kg was lethargic on Days 12, 13, and 14 of the study. Increased skin turgor was observed in 1 cat at 3 mg/kg on Days 10 and 11, 1 cat at 3 mg/kg on Day 12, and 1 cat at 5 mg/kg on Day 12. At gross necropsy, there were no treatment-related findings. Histopathologic evaluation of injection sites revealed a dose dependent inflammatory response

Twenty-four healthy domestic shorthair cats (12 males and 12 females) approximately 16 weeks of age were administered maropitant at 1 or 3 mg/kg, or saline at 0.1 mL/kg intravenously once daily for 5 days. Maropitant citrate injectable solution was administered at room temperature over 1-2 minutes. Reaction to injection was not specifically recorded, but one cat experienced discomfort with accidental extravascular administration. There were no clinically relevant findings during the study, at necropsy or in histopathology.

STORAGE CONDITIONS:

Emeprev™ (maropitant citrate) Injectable Solution should be stored at or below 30°C (86°F), with excursions permitted up to 40°C (104°F). After first vial puncture, store at or below 30ºC (86ºF). Use within 90 days of first puncture and puncture a maximum of 25 times.

HOW SUPPLIED:

Emeprev Injectable Solution is supplied in 20 mL amber glass vials. Each mL contains 10 mg of maropitant as maropitant citrate.

Approved by FDA under ANADA # 200-710

REFERENCES:

1. Diemunsch P, Grelot L. Potential of substance P antagonists as antiemetics. [Review] [60 refs]. Drugs. 2000;60:533-46.

Manufactured for:
Dechra Veterinary Products
7015 College Boulevard, Suite 525
Overland Park, KS 66211 USA

Emeprev is a trademark of Dechra Limited.

Rev. October 2025
1000010939

PRINCIPAL DISPLAY PANEL - 20 mL Vial

NDC 17033-004-01

EmeprevTM
(maropitant citrate)
Injectable Solution

10mg/mL maropitant

Antiemetic

For subcutaneous or intravenous injection in dogs and cats

CAUTION: Federal law restricts this drug to use by or on the order of a licensed veterinarian.

Approved by FDA under ANADA # 200-710

NET CONTENTS: 20 mL

Dechra